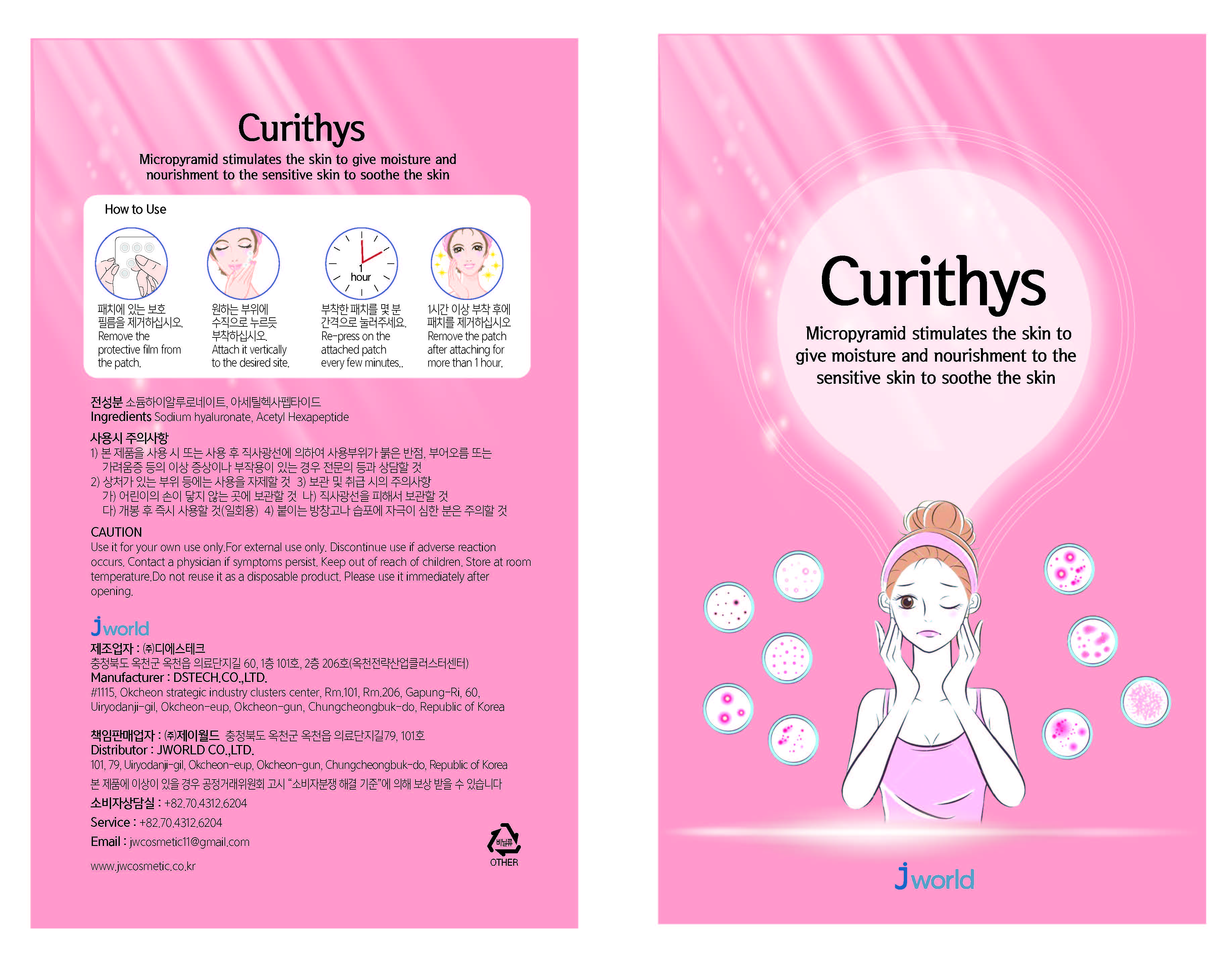 DRUG LABEL: CURITHYS
NDC: 72945-0002 | Form: PATCH
Manufacturer: J World
Category: otc | Type: HUMAN OTC DRUG LABEL
Date: 20211201

ACTIVE INGREDIENTS: HYALURONATE SODIUM 94.39 mg/100 mg
INACTIVE INGREDIENTS: NIACINAMIDE

Drug Facts

ACTIVE INGREDIENT

Sodium hyaluronate

INACTIVE INGREDIENT

Niacinamide
Salicylic Acid
Sh-Oligopepide-1
Sh-Polypepide-1
TetraPeptide-44
Centella Asiatica Extract
Tranexamic acid
Camellia Japonica Flower Extract

PURPOSE

Micro-pyramid stimulates the skin and gives moisture and nutrition to sensitive skin.

keep out of reach of the children

INDICATIONS AND USAGE

Remove the protective film from the patch.

Attach it vertically to the desired site.

Re-press on thea ttached patch every few minutes..

Remove the patch after attaching for more than 1 hour.

WARNINGS

Use it for your own use only.

For external use only.

Discontinue use if adverse reaction occurs.

Contact a physician if symptoms persist.

Store at room temperature

.Do not reuse it as a disposable product.

Please use it immediately after opening.

DOSAGE AND ADMINISTRATION

for topical use only